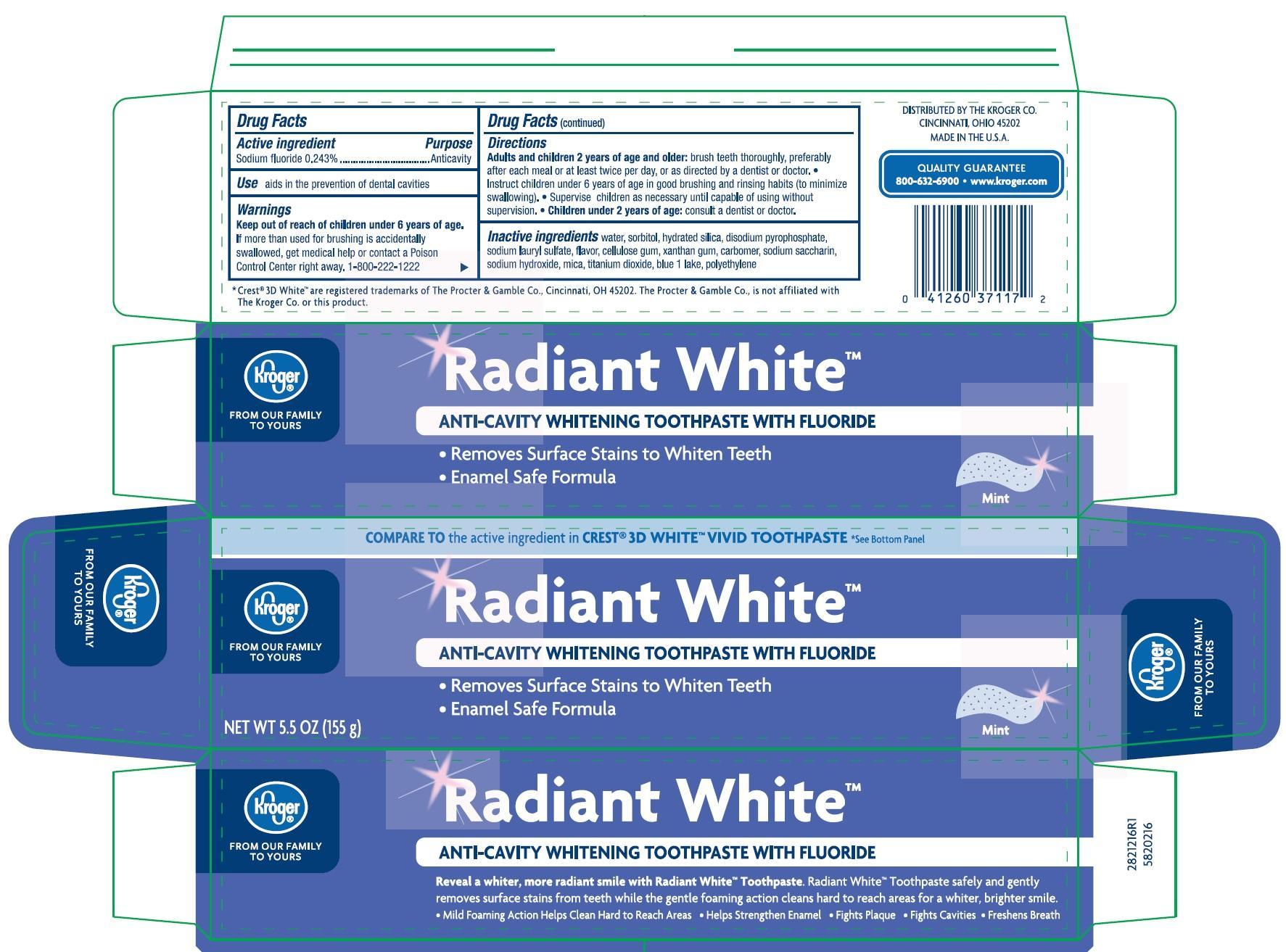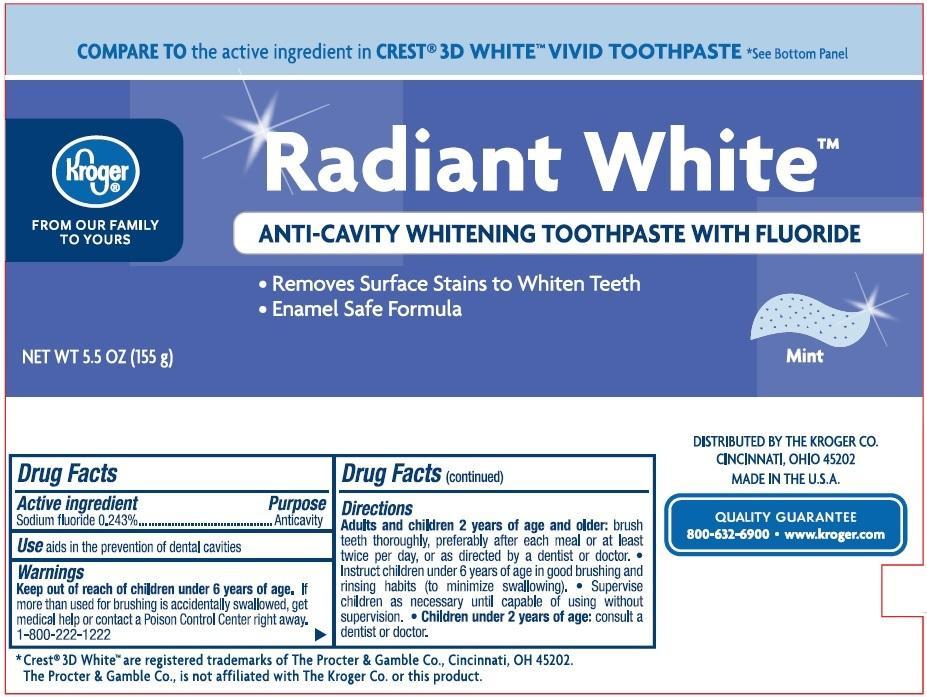 DRUG LABEL: Kroger Company
NDC: 30142-621 | Form: PASTE, DENTIFRICE
Manufacturer: Kroger Company
Category: otc | Type: HUMAN OTC DRUG LABEL
Date: 20230111

ACTIVE INGREDIENTS: SODIUM MONOFLUOROPHOSPHATE 0.76 g/100 g
INACTIVE INGREDIENTS: GLYCERIN; SODIUM PYROPHOSPHATE; POLYETHYLENE GLYCOL 600; PROPYLENE GLYCOL; SACCHARIN SODIUM; SUCRALOSE; BUTYLATED HYDROXYTOLUENE; PEG/PPG-116/66 COPOLYMER; PHOSPHORIC ACID; HYDRATED SILICA; HYDROGEN PEROXIDE

Drug Facts

Active ingredient

Sodium Monofluorophosphate 0.76% w/w (0.15% w/v fluoride ion)..................................Purpose: Anticavity

Uses

aids in the prevention of dental caviites

WARNINGS

If more than used for brushing is accidentally swallowed, get medical help or contact a Poison Control Center right away.

Keep out of reach of children under 6 years of age.

Directions

Adults and children 2 years of age and older: brush teeth thorughly preferably after each meal or at least twice a day, or as directed by a dentist or doctor. Instruct children under 6 years of age in good brushing and rinsing habits (to avoid swallowing). Supervise children as necessary until capable of using without supervision.

Other Information

Store in a cool dry place. Keep tube capped when not in use.

Inactive ingredients

glycerin, dicalcium phosphate, PEG-12, PVP, PEG/PPG 116/66 copolymer, hydrated silica, hydrogen peroxide, propylene glycol, flavor, sodium lauryl sulfate, tetrasodium pyrophosphate, sodium saccharin, phosphoric acid, sucralose, butylated hydroxytoluene, water

DOSAGE AND ADMINISTRATION

Adults and children 2 years of age and older: brush teeth throuoghly, preferably after every meal or at least twice a day, or as directed by a dentist or doctor.

PACKAGE LABEL

mm1.jpg

mm2.jpg